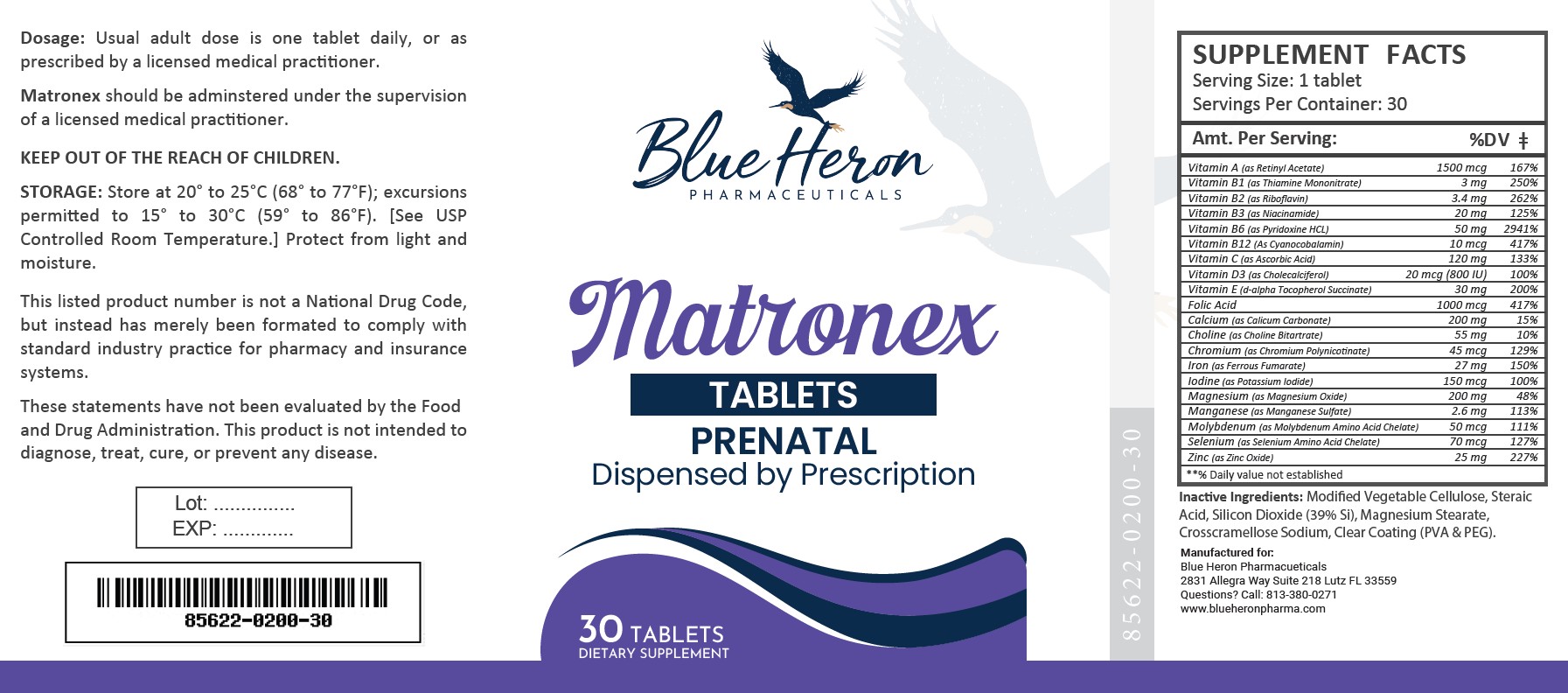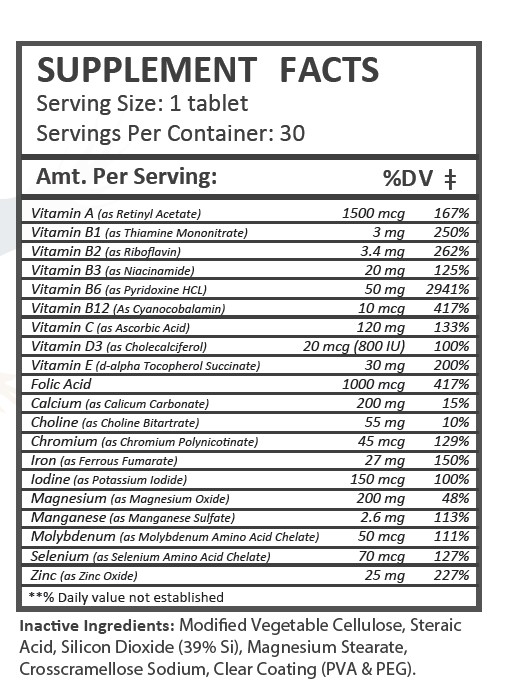 DRUG LABEL: Matronex
NDC: 85622-200 | Form: TABLET
Manufacturer: Blue Heron Pharmaceuticals, LLC
Category: prescription | Type: HUMAN PRESCRIPTION DRUG LABEL
Date: 20251014

ACTIVE INGREDIENTS: VITAMIN A ACETATE 1500 ug/1 1; THIAMINE MONONITRATE 3 mg/1 1; RIBOFLAVIN 3.4 mg/1 1; NIACINAMIDE 20 mg/1 1; PYRIDOXINE HYDROCHLORIDE 50 mg/1 1; CYANOCOBALAMIN 10 ug/1 1; ASCORBIC ACID 120 mg/1 1; CHOLECALCIFEROL 20 ug/1 1; .ALPHA.-TOCOPHEROL ACETATE, DL- 30 mg/1 1; FOLIC ACID 1000 ug/1 1; CALCIUM CARBONATE 200 mg/1 1; CHOLINE BITARTRATE 55 mg/1 1; CHROMIUM NICOTINATE 45 ug/1 1; FERROUS FUMARATE 27 mg/1 1; POTASSIUM IODIDE 150 ug/1 1; MAGNESIUM OXIDE 20 mg/1 1; MANGANESE SULFATE 2.6 mg/1 1; MOLYBDENUM 50 ug/1 1; SELENIUM 70 ug/1 1; ZINC OXIDE 25 mg/1 1

Matronex

HEALTH CLAIM:

Matronex Prenatal Tablets

Dispensed by Prescription

DESCRIPTION:

Matronex Prenatal Tablets are brown, round tablets dispensed in plastic bottles of 30 ct.

85622-0200-30

Reserved for Professional Recommendation

Matronex Prenatal Tablets are an orally administered prescription vitamin to provide significant amounts of Vitamins B6, B12, C, D3, E, riboflavin, niacinamide, thiamine monoitrate, and folate to supplement the diet, and to help assure that nutritional deficiencies of these vitamines will not develop.

Matronex Prenatal Tablets should be administered under the supervision of a licensed medical practitioner.

This listed product is not a National Drug Code, but instead has merely been formatted to comply with standard industry practice for pharmacy and insurance computer systems.

These statements have not been evaluated by the Food and Drug Administration. This product is not intended to diagnose, treat, cure or prevent any disease.

All prescriptions using this product shall be pursuant to state statutes as applicable. This is not an Orange Book product. This product may be administered only under a physician’s supervision. There are no implied or explicit claims on therapeutic equivalence.

Manufactured for:

Blue Heron Pharmaceuticals

Lutz, FL 33559

INDICATIONS:

Matronex is indicated to provide vitamins and minerals to women throughout pregnancy and during the postnatal period for both lactating and non-lactating mothers, and throughout the childbearing years.

Matronex may be beneficial in improving the nutritional status of women prior to conception.

WARNINGS:

This product is contraindicated in patients with a known hypersensitivity to any of the ingredients; also, all iron compounds are contraindicated in patients with hemosiderosis, hemochromatosis, or hemolytic anemias. Pernicious anemia is a contraindication, as folic acid may obscure its signs and symptoms.

Accidental overdose of iron-containing products is a leading cause of fatal poisoning in children under 6. Keep this product out of reach of children. In case of accidental overdose, call a doctor or poison control center immediately. Administration of folic acid alone is improper therapy for pernicious anemia and other megaloblastic anemias in which vitamin B 12 is deficient.

Matronex Prenatal Vitamins should only be used under the direction and supervision of a licensed medical practitioner. Use with caution in patients that may have a medical condition, are pregnant, lactating, trying to conceive, under the age of 18, or taking medications.

These statements have not been evaluated by the Food and Drug Administration. This product is not intended to diagnose, treat, cure, or prevent any disease.

DOSAGE:

Adults (persons over 12 years of age) One (1) Matronex caplet daily, between meals, or as directed by a physician. Do not administer to children under the age of 12.

PRECAUTIONS:

Iron: Signs and Symptoms: Iron is toxic. Acute overdosage of iron may cause nausea and vomiting and, in severe cases, cardiovascular collapse and death. Other symptoms include pallor and cyanosis, melena, shock, drowsiness, and coma. The estimated overdose of orally ingested iron is 300 mg/kg body weight. When overdoses are ingested by children, severe reactions, including fatalities, have resulted. Pretrate should be stored beyond the reach of children to prevent against accidental iron poisoning.

CONTRAINDICATIONS
This product is contraindicated in patients with known hypersensitivity to any of the ingredients.

PRECAUTIONS
This product is contraindicated in patients with a known hypersensitivity to any of the ingredients.

ADVERSE REACTIONS
Allergic sensitizations have been reported following oral administration of folic acid. Consult your physician immediately if adverse side effects occur.

KEEP OUT OF THE REACH OF CHILDREN.

STORAGE:

Store at 20° to 25°C (68° to 77°F); excursions permitted to 15° to 30°C (59° to 86°F). [See USP Controlled Room Temperature.] Protect from light and moisture.